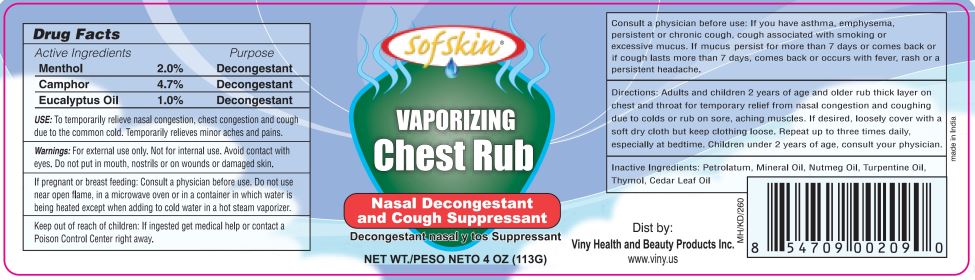 DRUG LABEL: Sof Skin Vaporizing Chest Rub and Cough Suppressant
NDC: 76436-127 | Form: GEL
Manufacturer: Viny Health and Beauty Inc
Category: otc | Type: HUMAN OTC DRUG LABEL
Date: 20250218

ACTIVE INGREDIENTS: CAMPHOR (NATURAL) 5.31 g/113 g; MENTHOL 2.26 g/113 g; EUCALYPTUS OIL 1.13 g/113 g
INACTIVE INGREDIENTS: MINERAL OIL; NUTMEG OIL; TURPENTINE; THYMOL; CEDAR LEAF OIL; PETROLATUM

VINY - Sof Skin Vaporizing Chest Rub and Cough Suppressant (76436-127)

Active Ingredients

Menthol 2.0%

Camphor 4.7%

Eucalyptus Oil 1.0%

Purpose

Decongestant

USE:

To temporarily relieve nasal congestion, chest congestion and cough due to the common cold. Temporarily relieves minor aches and pains.

Warnings:

For external use only. Not for internal use. Avoid contact with eyes. Do not put in mouth, nostrils or on wounds or damaged skin.

If pregnant or breast feeding:

Consult a physician before use.

Do not

use near open flame, in a microwave oven or in a container in which water is being heated except when adding to cold water in a hot steam vaporizer.

Keep out of reach of children:

If ingested get medical help or contact a Poison Control Center right away.

ASK DOCTOR

Consult a physician before use:

If you have asthma, emphysema, persistent or chronic cough, cough associated with smoking or excessive mucus. If muscle aches persist for more than 7 days or comes back or if cough lasts more than 7 days, comes back or occurs with fever, rash or a persistent headache.

Directions:

Adults and children 2 years of age and older rub thick layer on chest and throat for temporary relief from nasal congestion and coughing due to colds or rub on sore, aching muscles. if desired, loosely cover with a soft dry cloth but keep clothing loose. Repeat up to three times daily, especially at bedtime. Children under 2 years of age, consult your physician.

Inactive Ingredients:

Petrolatum, Mineral Oil, Nutmeg Oil, Turpentine Oil, Thymol, Cedar Leaf Oil